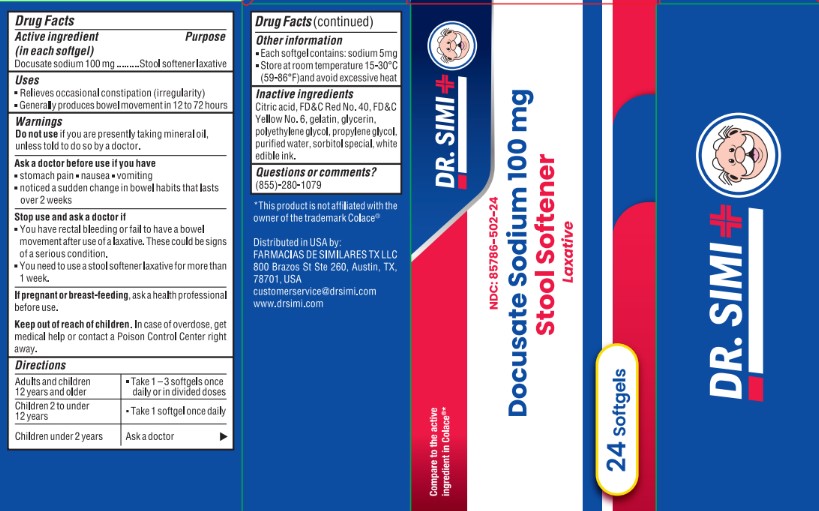 DRUG LABEL: DOCUSATE SODIUM 100MG
NDC: 85786-502 | Form: CAPSULE, LIQUID FILLED
Manufacturer: Farmacias De Similares TX LLC
Category: otc | Type: HUMAN OTC DRUG LABEL
Date: 20260128

ACTIVE INGREDIENTS: DOCUSATE SODIUM 100 mg/1 1
INACTIVE INGREDIENTS: GELATIN; GLYCERIN; ANHYDROUS CITRIC ACID; FD&C RED NO. 40; POLYETHYLENE GLYCOL, UNSPECIFIED; SORBITOL; PROPYLENE GLYCOL; FD&C YELLOW NO. 6; WATER

Active ingredient (in each softgel)

Docusate sodium 100 mg

Purpose

Stool softener laxative

Uses

. Relieves occasional constipation (irregularity)
. Generally produces bowel movement in 12 to 72 hours

Warnings

Do not use if

if you are presently taking mineral oil, unless directed to so by a doctor.

Ask a doctor before use if you have

. stomach pain - nausea . vomiting . noticed a sudden change in bowel habits that lasts over 2 weeks

Stop use and ask a doctor if

. You have rectal bleeding or fail to have a bowel movement after use of a laxative. These could be signs of a serious condition.
. You need to use a stool softener laxative for more than 1 week.

If pregnant or breast-feeding,

ask a health professional before use

Keep out of reach of children.

In case of overdose,

get medical help or contact a Poison Control Center right away.

Directions

Adults and children 12 years and older - Take 1-3 softgels once daily or in divided doses

Children under 12 years old - Take 1 softgel once daily
Children under 2 years - Ask a doctor

Other information

. Each softgel contains: sodium 5mg
. Store at room temperature 15-30°C (59-86°F)and avoid excessive heat

Inactive ingredients

Citric acid, FD&C Red No. 40, FD&C Yellow No. 6, gelatin, glycerin, polyethylene glycol, propylene glycol, purified water, sorbitol special, white edible ink.

Questions or comments?

(855)-280-1079

*This product is not affiliated with the owner of the trademark Colace®

Distributed in USA by:
FARMACIAS DE SIMILARES TX LLC
800 Brazos St Ste 260, Austin, TX,
78701, USA
customerservice@drsimi.com
www.drsimi.com

PACKAGE LABEL

Dr. Simi

Compare to the active ingredient in Colace®*

NDC: 85786-502-24
Docusate Sodium 100 mg

Stool Softener

Laxative

24 softgels